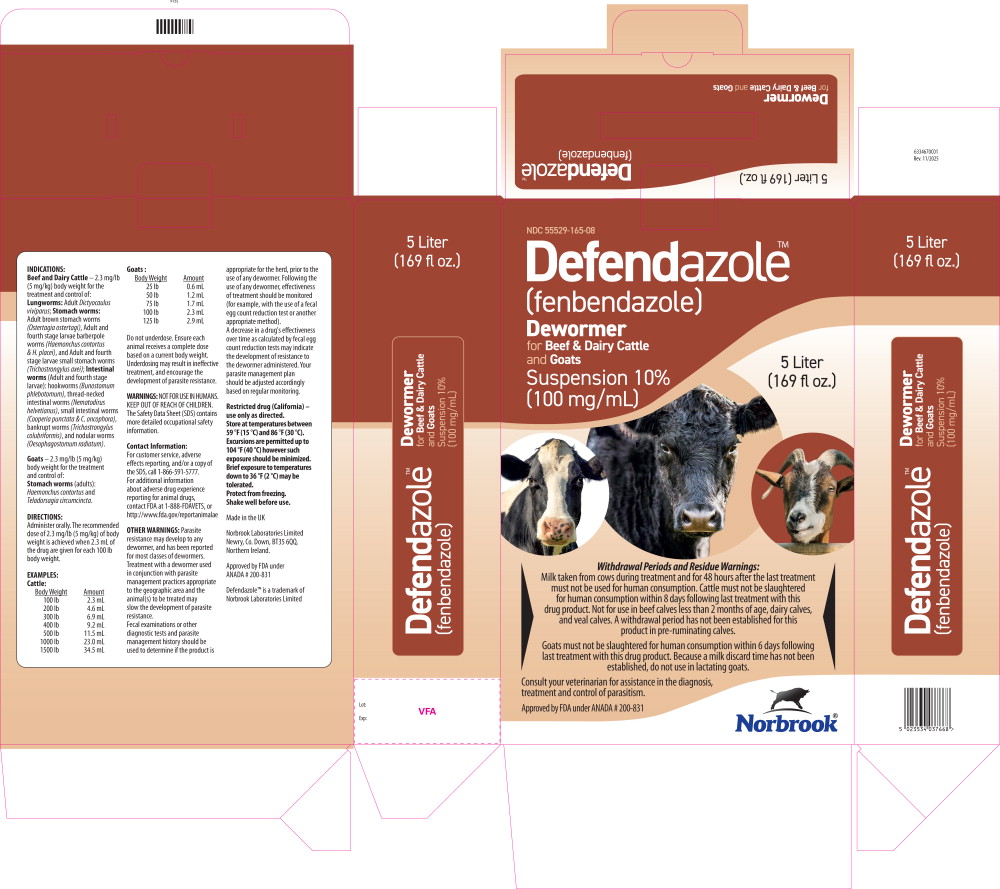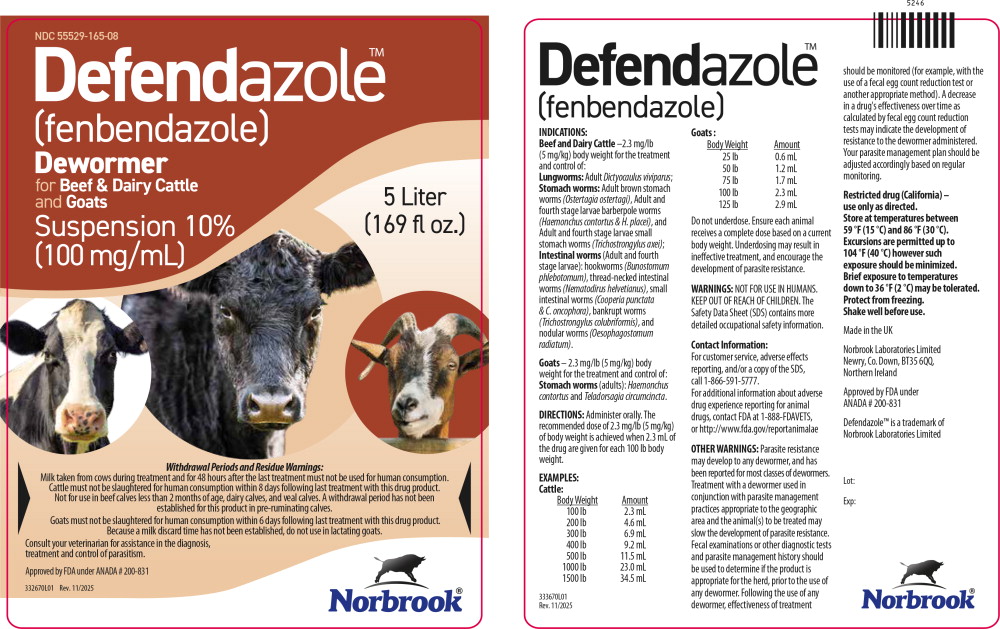 DRUG LABEL: Defendazole
NDC: 55529-165 | Form: SUSPENSION
Manufacturer: Norbrook Laboratories Limited
Category: animal | Type: OTC ANIMAL DRUG LABEL
Date: 20260115

ACTIVE INGREDIENTS: FENBENDAZOLE 100 mg/1 mL

INDICATIONS:

Beef and Dairy Cattle – 2.3 mg/lb (5 mg/kg) body weight for the treatment and control of: Lungworms: Adult Dictyocaulus viviparus; Stomach worms: Adult brown stomach worms (Ostertagia ostertagi), Adult and fourth stage larvae barberpole worms (Haemonchus contortus & H. placei), and Adult and fourth stage larvae small stomach worms (Trichostrongylus axei); Intestinal worms (Adult and fourth stage larvae): hookworms (Bunostomum phlebotomum), thread-necked intestinal worms (Nematodirus helvetianus), small intestinal worms (Cooperia punctata & C. oncophora), bankrupt worms (Trichostrongylus colubriformis), and nodular worms (Oesophagostomum radiatum).

Goats – 2.3 mg/lb (5 mg/kg) body weight for the treatment and control of: Stomach worms (adults): Haemonchus contortus and Teladorsagia circumcincta.

DIRECTIONS:

Administer orally. The recommended dose of 2.3 mg/lb (5 mg/kg) of body weight is achieved when 2.3 mL of the drug are given for each 100 lb body weight.

EXAMPLES:

Cattle:

Body Weight | Amount
100 lb | 2.3 mL
200 lb | 4.6 mL
300 lb | 6.9 mL
400 lb | 9.2 mL
500 lb | 11.5 mL
1000 lb | 23.0 mL
1500 lb | 34.5 mL

Goats :

Body Weight | Amount
25 lb | 0.6 mL
50 lb | 1.2 mL
75 lb | 1.7 mL
100 lb | 2.3 mL
125 lb | 2.9 mL

Do not underdose. Ensure each animal receives a complete dose based on a current body weight. Underdosing may result in ineffective treatment, and encourage the development of parasite resistance.

WARNINGS:

NOT FOR USE IN HUMANS.
KEEP OUT OF REACH OF CHILDREN.

The Safety Data Sheet (SDS) contains more detailed occupational safety information.

Contact Information:

For customer service, adverse effects reporting, and/or a copy of the SDS, call 1-866-591-5777.

For additional information about adverse drug experience reporting for animal drugs, contact FDA at 1-888-FDAVETS, or http://www.fda.gov/reportanimalae

OTHER WARNINGS:

Parasite resistance may develop to any dewormer, and has been reported for most classes of dewormers.

Treatment with a dewormer used in conjunction with parasite management practices appropriate to the geographic area and the animal(s) to be treated may slow the development of parasite resistance.

Fecal examinations or other diagnostic tests and parasite management history should be used to determine if the product is appropriate for the herd, prior to the use of any dewormer. Following the use of any dewormer, effectiveness of treatment should be monitored (for example, with the use of a fecal egg count reduction test or another appropriate method).

A decrease in a drug's effectiveness over time as calculated by fecal egg count reduction tests may indicate the development of resistance to the dewormer administered. Your parasite management plan should be adjusted accordingly based on regular monitoring.

Restricted drug (California) – use only as directed.

Store at temperatures between 59 °F (15 °C) and 86 °F (30 °C).

Excursions are permitted up to 104 °F (40 °C) however such exposure should be minimized. Brief exposure to temperatures down to 36 °F (2 °C) may be tolerated.

Protect from freezing. Shake well before use.

Withdrawal Periods and Residue Warnings:

Milk taken from cows during treatment and for 48 hours after the last treatment must not be used for human consumption. Cattle must not be slaughtered for human consumption within 8 days following last treatment with this drug product. Not for use in beef calves less than 2 months of age, dairy calves, and veal calves. A withdrawal period has not been established for this product in pre-ruminating calves.

Goats must not be slaughtered for human consumption within 6 days following last treatment with this drug product. Because a milk discard time has not been established, do not use in lactating goats.

Consult your veterinarian for assistance in the diagnosis, treatment and control of parasitism.

Made in the UK

Norbrook Laboratories Limited
Newry, Co. Down, BT35 6QQ,
Northern Ireland.

Approved by FDA under ANADA # 200-831

Defendazole™ is a trademark of Norbrook Laboratories Limited

Principal Display Panel - 100 mg/mL Carton Label

NDC 55529-165-08

Defendazole™
(fenbendazole)

Dewormer
for Beef & Dairy Cattle
and Goats

Suspension 10%
(100 mg/mL)

5 Liter
(169 fl oz.)

Norbrook®

Principal Display Panel - 100 mg/mL Jug Label

NDC 55529-165-08

Defendazole™
(fenbendazole)

Dewormer
for Beef & Dairy Cattle
and Goats

Suspension 10%
(100 mg/mL)

5 Liter
(169 fl oz.)

Norbrook®